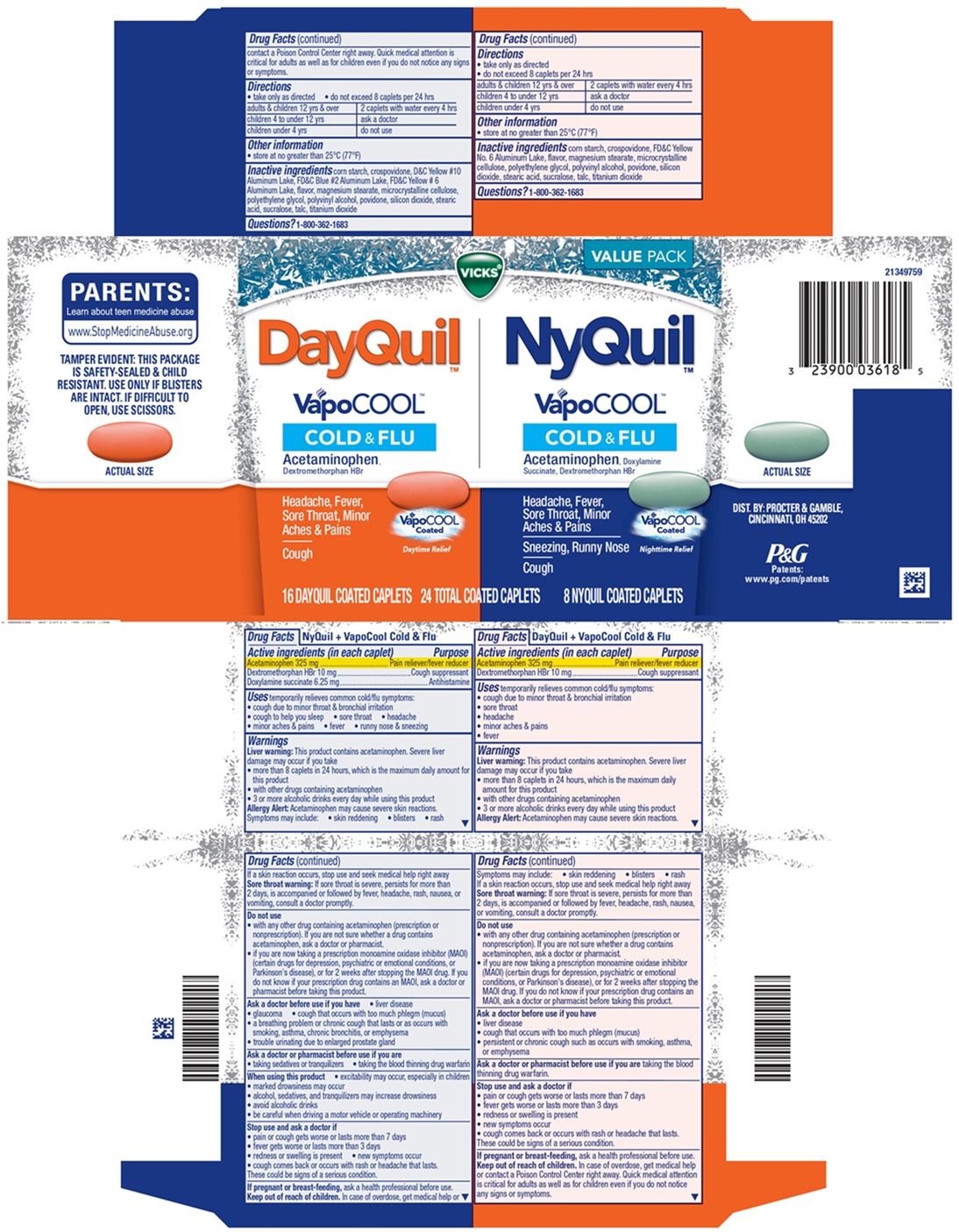 DRUG LABEL: Vicks DayQuil and Nyquil VapoCOOL
NDC: 84126-354 | Form: KIT | Route: ORAL
Manufacturer: The Procter & Gamble Manufacturing Company
Category: otc | Type: HUMAN OTC DRUG LABEL
Date: 20260123

ACTIVE INGREDIENTS: ACETAMINOPHEN 325 mg/1 1; DEXTROMETHORPHAN HYDROBROMIDE 10 mg/1 1; ACETAMINOPHEN 325 mg/1 1; DOXYLAMINE SUCCINATE 6.25 mg/1 1; DEXTROMETHORPHAN HYDROBROMIDE 10 mg/1 1
INACTIVE INGREDIENTS: STARCH, CORN; MICROCRYSTALLINE CELLULOSE; MAGNESIUM STEARATE; FD&C YELLOW NO. 6 ALUMINUM LAKE; SILICON DIOXIDE; TITANIUM DIOXIDE; STEARIC ACID; POLYVINYL ALCOHOL; SUCRALOSE; TALC; POVIDONE; CROSPOVIDONE; POLYETHYLENE GLYCOL, UNSPECIFIED; FD&C YELLOW NO. 6 ALUMINUM LAKE; SUCRALOSE; TALC; MICROCRYSTALLINE CELLULOSE; POLYVINYL ALCOHOL; SILICON DIOXIDE; STEARIC ACID; D&C YELLOW NO. 10 ALUMINUM LAKE; FD&C BLUE NO. 2 ALUMINUM LAKE; POVIDONE; MAGNESIUM STEARATE; POLYETHYLENE GLYCOL, UNSPECIFIED; TITANIUM DIOXIDE; STARCH, CORN; CROSPOVIDONE

Vicks® DayQuil™ & Nyquil™ VapoCOOL COLD & FLU, Coated Caplets

VICKS DayQuil VapoCOOL COLD & FLU, Coated Caplets

Active ingredients (in each caplet)

Acetaminophen 325 mg
Dextromethorphan HBr 10 mg

Purpose

Pain reliever/Fever reducer

Cough suppressant

Uses

temporarily relieves common cold/flu symptoms:

- cough due to minor throat & bronchial irritation
- sore throat
- headache
- minor aches & pains
- fever

Warnings

Liver warning:

This product contains acetaminophen. Severe liver damage may occur if you take

- more than 8 caplets in 24 hours, which is the maximum daily amount for this product
- with other drugs containing acetaminophen
- 3 or more alcoholic drinks every day while using this product

Allergy Alert:

Acetaminophen may cause severe skin reactions. Symptoms may include:

- Skin reddening
- Blisters
- Rash

If a skin reaction occurs, stop use and seek medical help right away

Sore throat warning:

If sore throat is severe, persists for more than 2 days, is accompanied or followed by fever, headache, rash, nausea, or vomiting, consult a doctor promptly.

Do not use

- with any other drug containing acetaminophen (prescription or nonprescription). If you are not sure whether a drug contains acetaminophen, ask a doctor or pharmacist.
- if you are now taking a prescription monoamine oxidase inhibitor (MAOI) (certain drugs for depression, psychiatric or emotional conditions, or Parkinson's disease), or for 2 weeks after stopping the MAOI drug. If you do not know if your prescription drug contains an MAOI, ask a doctor or pharmacist before taking this product.

Ask a doctor before use if you have

- liver disease
- cough that occurs with too much phlegm (mucus)
- persistent or chronic cough such as occurs with smoking, asthma, chronic bronchitis, or emphysema

Ask a doctor or pharmacist before use if you are

taking the blood thinning drug warfarin.

Stop use and ask a doctor if

- pain or cough gets worse or lasts more than 7 days
- fever gets worse or lasts more than 3 days
- redness or swelling is present
- new symptoms occur
- cough comes back or occurs with rash or headache that lasts.
  These could be signs of a serious condition.

If pregnant or breast-feeding,

ask a health professional before use.

Keep out of reach of children.

OVERDOSAGE

In case of overdose, get medical help or contact a Poison Control Center right away. Quick medical attention is critical for adults as well as for children even if you do not notice any signs or symptoms.

Directions

- take only as directed
- do not exceed 8 caplets per 24 hrs

adults & children 12 yrs & over | 2 caplets with water every 4 hrs
children 4 to under 12 yrs | ask a doctor
children under 4 yrs | do not use

Other information

- store at no greater than 25°C (77ºF)

Inactive ingredients

corn starch, crospovidone, FD&C Yellow No. 6 Aluminum Lake, flavor, magnesium stearate, microcrystalline cellulose, polyethylene glycol, polyvinyl alcohol, povidone, silicon dioxide, stearic acid, sucralose, talc, titanium dioxide

Questions?

1-800-362-1683

Vicks NyQuil VapoCOOL COLD & FLU, Coated Caplets

Active ingredients (in each caplet)

Acetaminophen 325 mg
Dextromethorphan HBr 10 mg
Doxylamine succinate 6.25 mg

Purpose

Pain reliever/Fever reducer
Cough suppressant
Antihistamine

Uses

temporarily relieves common cold/flu symptoms:

- cough due to minor throat & bronchial irritation
- cough to help you sleep
- sore throat
- headache
- minor aches & pains
- fever
- runny nose & sneezing

Warnings

Liver warning:

This product contains acetaminophen. Severe liver damage may occur if you take

- more than 8 caplets in 24 hours, which is the maximum daily amount for this product
- with other drugs containing acetaminophen
- 3 or more alcoholic drinks every day while using this product

Allergy Alert:

Acetaminophen may cause severe skin reactions. Symptoms may include:

- Skin reddening
- Blisters
- Rash

If a skin reaction occurs, stop use and seek medical help right away

Sore throat warning:

If sore throat is severe, persists for more than 2 days, is accompanied or followed by fever, headache, rash, nausea, or vomiting, consult a doctor promptly.

Do not use

- with any other drug containing acetaminophen (prescription or nonprescription). If you are not sure whether a drug contains acetaminophen, ask a doctor or pharmacist.
- if you are now taking a prescription monoamine oxidase inhibitor (MAOI) (certain drugs for depression, psychiatric or emotional conditions, or Parkinson's disease), or for 2 weeks after stopping the MAOI drug. If you do not know if your prescription drug contains an MAOI, ask a doctor or pharmacist before taking this product.

Ask a doctor before use if you have

- liver disease
- glaucoma
- cough that occurs with too much phlegm (mucus)
- a breathing problem or chronic cough that lasts or as occurs with smoking, asthma, chronic bronchitis, or emphysema
- trouble urinating due to enlarged prostate gland

Ask a doctor or pharmacist before use if you are

- taking sedatives or tranquilizers
- taking the blood thinning drug warfarin

When using this product

- excitability may occur, especially in children
- marked drowsiness may occur
- alcohol, sedatives, and tranquilizers may cause drowsiness
- avoid alcoholic drinks
- be careful when driving a motor vehicle or operating machinery

Stop use and ask a doctor if

- pain, nasal congestion, or cough gets worse or lasts more than 7 days
- fever gets worse or lasts more than 3 days
- redness or swelling is present
- new symptoms occur
- cough comes back or occurs with rash or headache that lasts.
  These could be signs of a serious condition.

If pregnant or breast-feeding,

ask a health professional before use.

Keep out of reach of children.

OVERDOSAGE

In case of overdose, get medical help or contact a Poison Control Center right away. Quick medical attention is critical for adults as well as for children even if you do not notice any signs or symptoms.

Directions

- take only as directed
- do not exceed 8 caplets per 24 hrs

adults & children 12 yrs & over | 2 caplets with water every 4 hrs
children 4 to under 12 yrs | ask a doctor
children under 4 yrs | do not use

Other information

- store at no greater than 25°C (77°F)

Inactive ingredients

corn starch, D&C Yellow #10 Aluminum Lake, FD&C Blue #2 Aluminum Lake, FD&C Yellow #6 Aluminum Lake, flavor, magnesium stearate, microcrystaline cellulose, polyethylene glycol, polyvinyl alcohol, povidone, silicon dioxide, stearic acid, sucralose, talc, titanium dioxide

Questions?

1-800-362-1683

TAMPER EVIDENT: THIS PACKAGE IS SAFETY-SEALED & CHILD RESISTANT. USE ONLY IF BLISTERS ARE INTACT. IF DIFFICULT TO OPEN, USE SCISSORS.

DIST. BY PROCTER & GAMBLE,
CINCINNATI, OH 45202.

PRINCIPAL DISPLAY PANEL - Kit Carton

Vicks®

DayQuil™ VapoCOOL™ COLD & FLU + CONGESTION

Acetaminophen, Dextromethorphan HBr

Headache, Fever, Sore Throat, Minor Aches & Pains

NyQuil™ VapoCOOL™ COLD & FLU + CONGESTION

Acetaminophen, Doxylamine Succinate, Dextromethorphan HBr

Headache, Fever, Sore Throat, Minor Aches & Pains

16 DAYQUIL COATED CAPLETS, 8 NYQUIL COATED CAPLETS: 24 TOTAL COATED CAPLETS